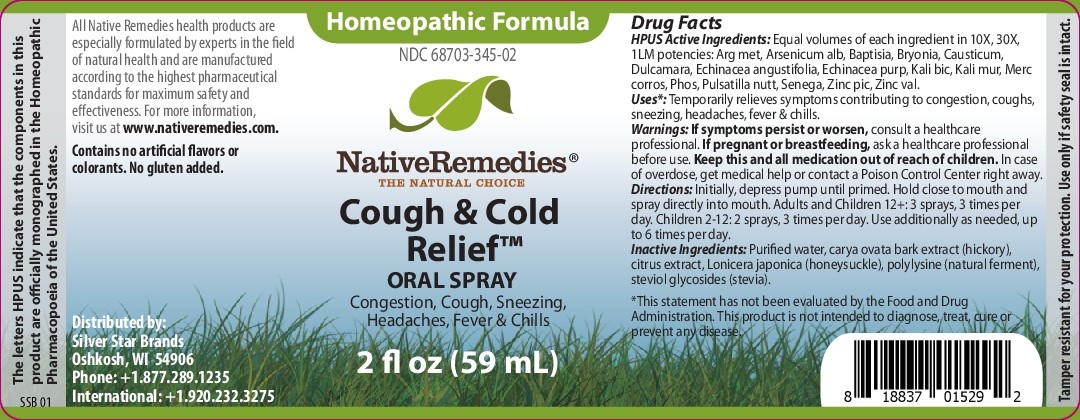 DRUG LABEL: Cough and Cold Relief
NDC: 68703-345 | Form: SPRAY
Manufacturer: Silver Star Brands
Category: homeopathic | Type: HUMAN OTC DRUG LABEL
Date: 20241203

ACTIVE INGREDIENTS: PHOSPHORUS 10 [hp_X]/59 mL; ZINC PICRATE 10 [hp_X]/59 mL; POLYGALA SENEGA ROOT 10 [hp_X]/59 mL; ZINC VALERATE 10 [hp_X]/59 mL; MERCURIC CHLORIDE 10 [hp_X]/59 mL; ARSENIC TRIOXIDE 10 [hp_X]/59 mL; POTASSIUM DICHROMATE 10 [hp_X]/59 mL; BAPTISIA TINCTORIA 10 [hp_X]/59 mL; CAUSTICUM 10 [hp_X]/59 mL; ECHINACEA PURPUREA 10 [hp_X]/59 mL; ANEMONE PATENS WHOLE 10 [hp_X]/59 mL; ECHINACEA ANGUSTIFOLIA 10 [hp_X]/59 mL; POTASSIUM CHLORIDE 10 [hp_X]/59 mL; SILVER 10 [hp_X]/59 mL; SOLANUM DULCAMARA FLOWER 10 [hp_X]/59 mL
INACTIVE INGREDIENTS: GLUCOSYL STEVIOL; POLY-L-LYSINE (30000-70000 MW); WATER; CARYA OVATA BARK; LONICERA JAPONICA FLOWER; ANHYDROUS CITRIC ACID

NativeRemedies® Cough & Cold Relief Oral Spray

HPUS Active Ingredients: Equal volumes of each ingredientin 10X, 30x, 1LM potencies; Arg met, Arsenicum alb, Baptisia, Bryonia, Causticum, Dulcamara, Echinacea angustifolia, Echinacea purp, Kali bic, kali mur, merc corros, Phos, Pulsatilla nutt, Senega, zinc pic, Zinc val.

Uses*

Temporarily relieves symptoms contributing to congestion, coughs, sneezing, headaches, fever & chills.

*This statement has not been evaluated by the Food and drug Administration. This product is not intended to diagnose, treat, cure or prevent any disease.

Warnings

Warnings: If symptom spersist or worsen, consult a healthcare professional. If pregnant or breastfeeding, ask a healthcare professional before use. Keep this and all medication out of reach of children. in case of overdose, get medical help or contact a Poison Control Center right away.

Directions

Directions: Initially, depress pump until primed. Hold close to mouth and spray directly into mouth. Adults and Children 12+: 3 sprays, 3 times per day. childeren 2-12: 2 sprays, 3 times perday. Use additionally as needed, up to 6 times per day.

OTHER SAFETY INFORMATION

Contains no artificial flavors or colorants. No gluten added.

Tamper resistant for your protection. Use only if saftey seal is intact.

Inactive Ingredients

Inactive ingredients: Purified water, carya ovata bark extract (hickory), citrus extract, Lonicera japonica (honeysuckle), polylysine (natural ferment), steviol glycosides (stevia).

KEEP OUT OF REACH OF CHILDREN

Keep this and all medication out of reach of children.

PREGNANCY OR BREAST FEEDING

If pregnant or breastfeeding, as ka healthcare professional before use.

PURPOSE

Congestion, Cough, Sneezing, Headaches, Fever & Chills.